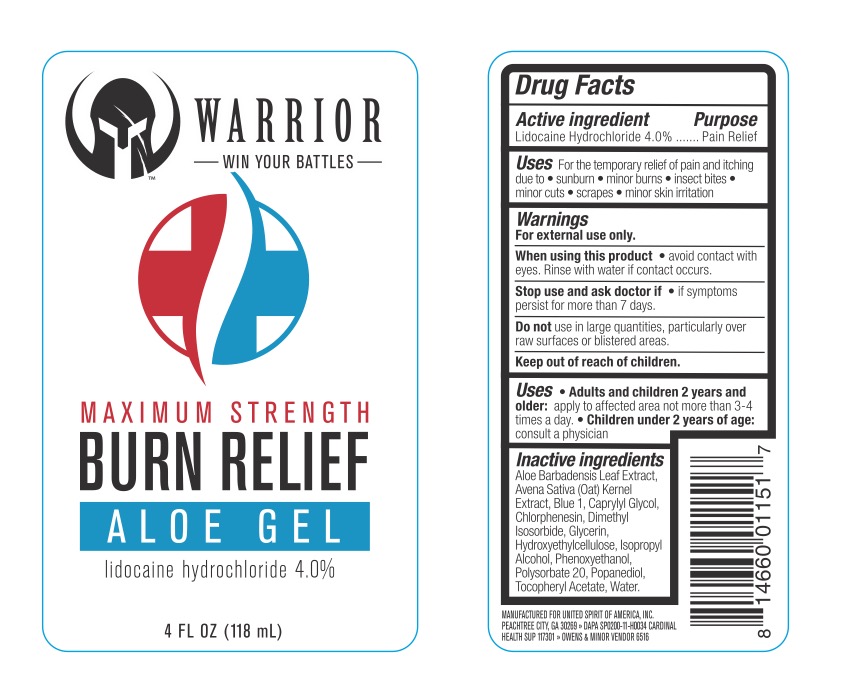 DRUG LABEL: Warrior Burn Relief Aloe
NDC: 72839-185 | Form: GEL
Manufacturer: Derma Care Research Labs, LLC
Category: otc | Type: HUMAN OTC DRUG LABEL
Date: 20241219

ACTIVE INGREDIENTS: LIDOCAINE HYDROCHLORIDE 4 g/100 mL
INACTIVE INGREDIENTS: ISOPROPYL ALCOHOL; PHENOXYETHANOL; CETYL HYDROXYETHYLCELLULOSE (350000 MW); GLYCERIN; ETHYLHEXYLGLYCERIN; POLYSORBATE 20; ALOE VERA LEAF; CHLORPHENESIN; WATER; CAPRYLYL GLYCOL; DIMETHYL ISOSORBIDE; OATMEAL; .ALPHA.-TOCOPHEROL ACETATE; FD&C BLUE NO. 1

Warrior Burn Relief Aloe Gel, 4% Lidocaine HCl

ACTIVE INGREDIENT

Lidocaine HCl 4%

PURPOSE

Pain Relief

DOSAGE AND ADMINISTRATION

For the temporary relief of pain and itching due to sunburn, minor burns, insect bites, minor cuts, scrapes, and minor skin irritation.

WARNINGS

For external use only.

When using this product avoid contact with eyes. Rinse with water if contact occurs. Stop use and ask a doctor if symptoms persist for more than 7 days. Do not use in large quantities, particularly over raw surfaces or blistered areas.

KEEP OUT OF REACH OF CHILDREN

In case of accidental ingestion, seek professional assistance or contact a Poison Control Center immediately.

INDICATIONS AND USAGE

Adults and children 2 years and older: apply to the affected area, not more than 3 to 4 times daily. Children under 2 years of age: ask a doctor.

INACTIVE INGREDIENT

Aloe Barbadensis Leaf Extract, Avena Sativa (Oat) Kernel Extract, Blue 1, Caprylyl Glycol, Chlorphenesin, Dimethyl Isosorbide, Glycerin, Hydroxyethylcellulose, Isopropyl Alcohol, Phenoxyethanol, Polysorbate 20, Propanediol, Tocopheryl Acetate, Water.